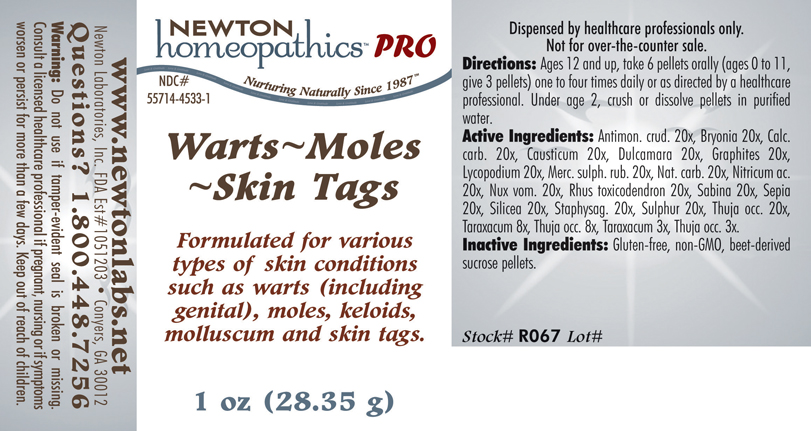 DRUG LABEL: Warts - Moles - Skin Tags 
NDC: 55714-4533 | Form: PELLET
Manufacturer: Newton Laboratories, Inc.
Category: homeopathic | Type: HUMAN PRESCRIPTION DRUG LABEL
Date: 20110601

ACTIVE INGREDIENTS: Antimony Trisulfide 20 [hp_X]/1 g; Bryonia Alba Root 20 [hp_X]/1 g; Oyster Shell Calcium Carbonate, Crude 20 [hp_X]/1 g; Causticum 20 [hp_X]/1 g; Solanum Dulcamara Top 20 [hp_X]/1 g; Graphite 20 [hp_X]/1 g; Lycopodium Clavatum Spore 20 [hp_X]/1 g; Mercuric Sulfide 20 [hp_X]/1 g; Sodium Carbonate 20 [hp_X]/1 g; Nitric Acid 20 [hp_X]/1 g; Strychnos Nux-vomica Seed 20 [hp_X]/1 g; Toxicodendron Pubescens Leaf 20 [hp_X]/1 g; Juniperus Sabina Leafy Twig 20 [hp_X]/1 g; Sepia Officinalis Juice 20 [hp_X]/1 g; Silicon Dioxide 20 [hp_X]/1 g; Delphinium Staphisagria Seed 20 [hp_X]/1 g; Sulfur 20 [hp_X]/1 g; Thuja Occidentalis Leafy Twig 20 [hp_X]/1 g; Taraxacum Officinale 8 [hp_X]/1 g
INACTIVE INGREDIENTS: Sucrose

Warts - Moles - Skin Tags

INDICATIONS & USAGE SECTION

Warts - Moles - Skin Tags Formulated for various types of skin conditions such as warts (including genital), moles, keloids, molluscum and skin tags.

DOSAGE & ADMINISTRATION SECTION

Directions: ORAL USE ONLY - SHAKE WELL. Ages 12 and up, take 6 pellets orally (ages 0 to 11, give 3 pellets) one to four times daily or as directed by a healthcare professional. Under age 2, crush or dissolve pellets in purified water.

ACTIVE INGREDIENT SECTION

Antimon. crud. 20x, Bryonia 20x, Calc.carb. 20x, Causticum 20x, Dulcamara 20x, Graphites 20x, Lycopodium 20x, Merc. sulph. rub. 20x, Nat. carb. 20x, Nitricum ac. 20x, Nux vom. 20x, Rhus toxicodendron 20x, Sabina 20x, Sepia 20x, Silicea 20x, Staphysag. 20x, Sulphur 20x, Thuja occ. 20x, Taraxacum 8x, Thuja occ. 8x, Taraxacum 3x, Thuja occ. 3x.

PURPOSE SECTION

Formulated for various types of skin conditions such as warts (including genital), moles, keloids, molluscum and skin tags.

INACTIVE INGREDIENT SECTION

Inactive Ingredients: Gluten-free, non-GMO, beet-derived sucrose pellets.

QUESTIONS? SECTION

www.newtonlabs.net Newton Laboratories, Inc. FDA Est # 1051203 - Conyers, GA 30012
Questions? 1.800.448.7256

WARNINGS SECTION

Warning: Do not use if tamper - evident seal is broken or missing. Consult a licensed healthcare professional if pregnant, nursing or if symptoms worsen or persist for more than a few days. Keep out of reach of children.

PREGNANCY OR BREAST FEEDING SECTION

Consult a licensed healthcare professional if pregnant, nursing or if symptoms worsen or persist for more than a few days

KEEP OUT OF REACH OF CHILDREN SECTION

Keep out of reach of children